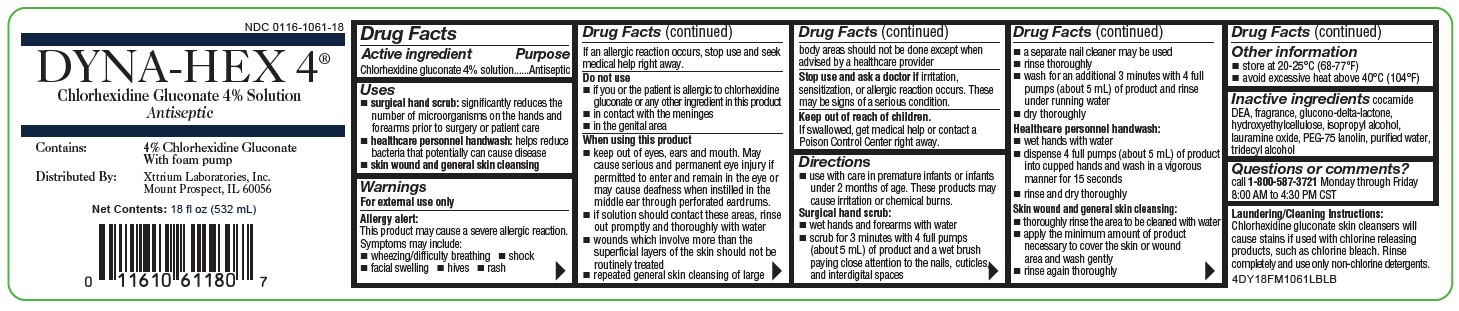 DRUG LABEL: DYNA-HEX 4
NDC: 0116-1060 | Form: LIQUID
Manufacturer: Xttrium Laboratories, Inc.
Category: otc | Type: HUMAN OTC DRUG LABEL
Date: 20231109

ACTIVE INGREDIENTS: CHLORHEXIDINE GLUCONATE 4 g/100 mL
INACTIVE INGREDIENTS: ISOPROPYL ALCOHOL; LAURAMINE OXIDE; PEG-75 LANOLIN; WATER; TRIDECYL ALCOHOL; COCO DIETHANOLAMIDE; GLUCONOLACTONE; HYDROXYETHYL CELLULOSE (140 CPS AT 5%)

4% Dyna-Hex, 18-oz

Active ingredient

Chlorhexidine gluconate 4% solution

Purpose

Antiseptic

Uses

- surgical hand scrub: significantly reduces the number of microorganisms on the hands and forearms prior to surgery or patient care
- healthcare personnel handwash: helps reduce bacteria that potentially can cause disease
- skin wound and general skin cleansing

Warnings

For external use only

Allergy alert:

This product may cause a severe allergic reaction. Symptoms may include:

- wheezing/difficulty breathing
- shock
- facial swelling
- hives
- rash

If an allergic reaction occurs, stop use and seek medical help right away.

Do not use

- if you are allergic to chlorhexidine gluconate or any other ingredient in this product

When using this product

- keep out of eyes, ears, and mouth. May cause serious and permanent eye injury if placed or kept in the eye during surgical procedures or may cause deafness when instilled in the middle ear through perforated eardrums.
- if solution should contact these areas, rinse out promptly and thoroughly with water
- do not use routinely if you have wounds which involve more than the superficial layers of the skin

Stop use and ask a doctor if

irritation, sensitization or allergic reaction occurs. These may be signs of a serious condition.

Keep out of reach of children.

If swallowed, get medical help or contact a Poison Control Center right away.

Directions

- use with care in premature infants or infants under 2 months of age. These products may cause irritation or chemical burns.

Surgical hand scrub:

- wet hands and forearms with water
- scrub for 3 minutes with 3 full pumps (5 grams) of product and a wet brush paying close attention to the nails, cuticles, and interdigital spaces
- a seperate nail cleaner may be used
- rinse thoroughly
- wash for an additional 3 minutes with 3 full pumps (5 grams) of product and rinse under running water
- dry thoroughly

Healthcare personnel handwash:

- wet hands with water
- dispense 3 full pumps (5 grams) of product into cupped hands and wash in a vigorous manner for 15 seconds
- rinse and dry thoroughly

Skin wound and general skin cleansing:
 thoroughly rinse the area to be cleaned with water
 apply the minimum amount of product necessary to cover the skin or wound
area and wash gently
 rinse again thoroughly

Other information

- store at 20-25°C (68-77°F)
- avoid excessive heat above 40°C (104°F)

Inactive ingredients

cocamide DEA, fragrance, glucono-delta-lactone, isopropyl alcohol, lauramine oxide, PEG-75 lanolin, purified water, tridecyl alcohol

Questions of Comments?

Call 1-800-587-3721 Monday through Friday 8:00 AM to 4:30 PM CST

RECENT MAJOR CHANGES

Indications and Usage

Dosage and Administration

addition of "skin wounf and general skin cleansing (11/23)

Laundering/Cleaning Instructions: Chlorhexidine gluconate skin cleansers will cause stains if used with chlorine releasing products, such as chlorine bleach. Rinse completely and use only non-chlorine detergents.

Package/Label Principal Display Panel

NDC 0116-1060-18

DYNA-HEX 4®

Chlorhexidine Gluconate 4% Solution

Antiseptic

Contains: 4% Chlorhexidine Gluconate With foam pump

Distributed By: Xttrium Laboratories, Inc. Mount Prospect, IL 60056

Net Contents: 18 fl oz (532 mL)

4DYN18BTLLBLB